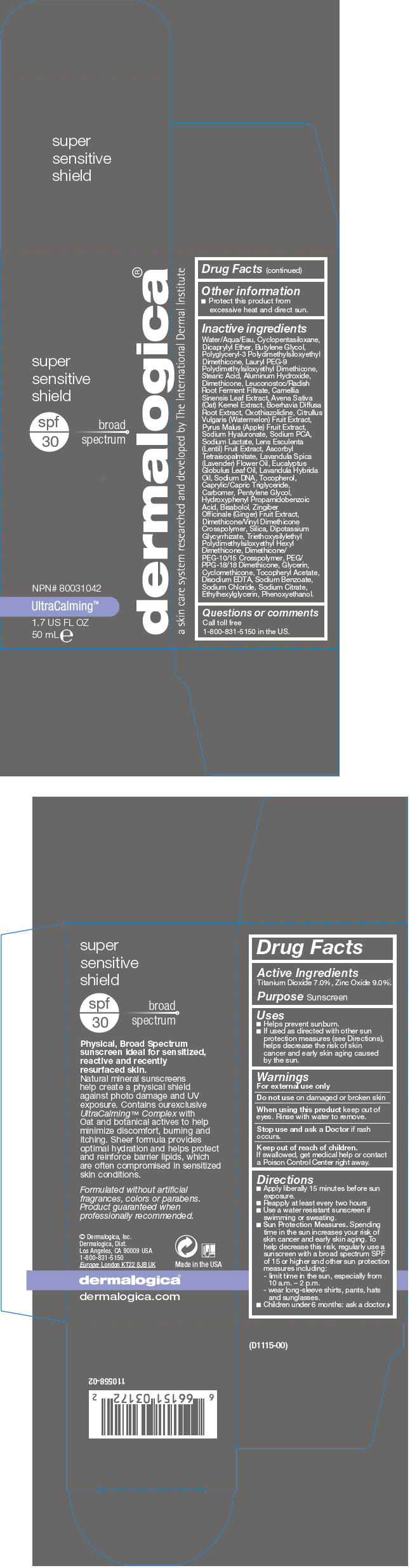 DRUG LABEL: Super Sensitive Shield 
NDC: 68479-150 | Form: LOTION
Manufacturer: Dermalogica, Inc.
Category: otc | Type: HUMAN OTC DRUG LABEL
Date: 20171206

ACTIVE INGREDIENTS: Titanium Dioxide 70 mg/1 mL; Zinc Oxide 90 mg/1 mL
INACTIVE INGREDIENTS: Water; Cyclomethicone 5; Dicaprylyl Ether; Butylene Glycol; Lauryl PEG-9 Polydimethylsiloxyethyl Dimethicone; Stearic Acid; Aluminum Hydroxide; Dimethicone; Leuconostoc/Radish Root Ferment Filtrate; Green Tea Leaf; Oat; Boerhavia Diffusa Root; Oxothiazolidine; Watermelon; Apple; Hyaluronate Sodium; Sodium Pyrrolidone Carboxylate; Sodium Lactate; Lens Culinaris Fruit; Ascorbyl Tetraisopalmitate; Lavender Oil; Eucalyptus Oil; Lavandin Oil; Tocopherol; Medium-Chain Triglycerides; Carbomer Homopolymer Type C (Allyl Pentaerythritol Crosslinked); Pentylene Glycol; Hydroxyphenyl Propamidobenzoic Acid; Levomenol; Ginger; Dimethicone/Vinyl Dimethicone Crosspolymer (Soft Particle); Silicon Dioxide; Glycyrrhizinate Dipotassium; PEG/PPG-18/18 Dimethicone; Glycerin; Cyclomethicone; .Alpha.-Tocopherol Acetate; Edetate Disodium; Sodium Benzoate; Sodium Chloride; Sodium Citrate, Unspecified Form; Ethylhexylglycerin; Phenoxyethanol

Super Sensitive Shield
SPF 30

Drug Facts

Active Ingredients

Titanium Dioxide 7.0%, Zinc Oxide 9.0%.

Purpose

Sunscreen

Uses

- Helps prevent sunburn.
- If used as directed with other sun protection measures (see Directions), helps decrease the risk of skin cancer and early skin aging caused by the sun.

Warnings

For external use only

Do not use on damaged or broken skin

When using this product keep out of eyes. Rinse with water to remove.

Stop use and ask a Doctor if rash occurs.

Keep out of reach of children.

If swallowed, get medical help or contact a Poison Control Center right away.

Directions

- Apply liberally 15 minutes before sun exposure.
- Reapply at least every two hours
- Use a water resistant sunscreen if swimming or sweating.
- Sun Protection Measures. Spending time in the sun increases your risk of skin cancer and early skin aging. To help decrease this risk, regularly use a sunscreen with a broad spectrum SPF of 15 or higher and other sun protection measures including:
  - limit time in the sun, especially from 10 a.m. – 2 p.m.
  - wear long-sleeve shirts, pants, hats and sunglasses.
- Children under 6 months: ask a doctor.

Other information

- Protect this product from excessive heat and direct sun.

Inactive ingredients

Water/Aqua/Eau, Cyclopentasiloxane, Dicaprylyl Ether, Butylene Glycol, Polyglyceryl-3 Polydimethylsiloxyethyl Dimethicone, Lauryl PEG-9 Polydimethylsiloxyethyl Dimethicone, Stearic Acid, Aluminum Hydroxide, Dimethicone, Leuconostoc/Radish Root Ferment Filtrate, Camellia Sinensis Leaf Extract, Avena Sativa (Oat) Kernel Extract, Boerhavia Diffusa Root Extract, Oxothiazolidine, Citrullus Vulgaris (Watermelon) Fruit Extract, Pyrus Malus (Apple) Fruit Extract, Sodium Hyaluronate, Sodium PCA, Sodium Lactate, Lens Esculenta (Lentil) Fruit Extract, Ascorbyl Tetraisopalmitate, Lavandula Spica (Lavender) Flower Oil, Eucalyptus Globulus Leaf Oil, Lavandula Hybrida Oil, Sodium DNA, Tocopherol, Caprylic/Capric Triglyceride, Carbomer, Pentylene Glycol, Hydroxyphenyl Propamidobenzoic Acid, Bisabolol, Zingiber Officinale (Ginger) Fruit Extract, Dimethicone/Vinyl Dimethicone Crosspolymer, Silica, Dipotassium Glycyrrhizate, Triethoxysilylethyl Polydimethylsiloxyethyl Hexyl Dimethicone, Dimethicone/ PEG-10/15 Crosspolymer, PEG/ PPG-18/18 Dimethicone, Glycerin, Cyclomethicone, Tocopheryl Acetate, Disodium EDTA, Sodium Benzoate, Sodium Chloride, Sodium Citrate, Ethylhexylglycerin, Phenoxyethanol.

Questions or comments

Call toll free
1-800-831-5150 in the US.

PRINCIPAL DISPLAY PANEL - 50 mL Bottle Carton

super
sensitive
shield

spf
30

broad
spectrum

NPN# 80031042

UltraCalming™

1.7 US FL OZ
50 mL e

dermalogica®